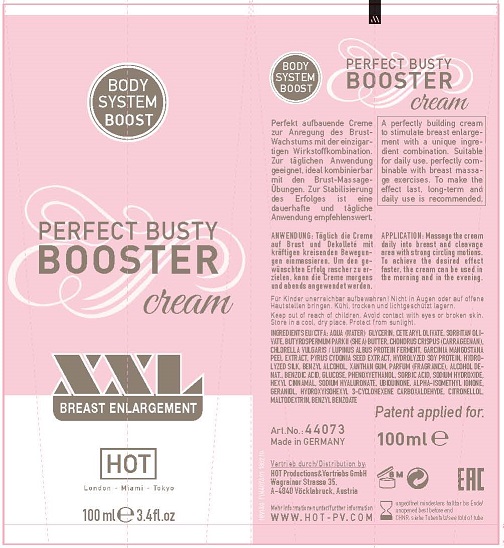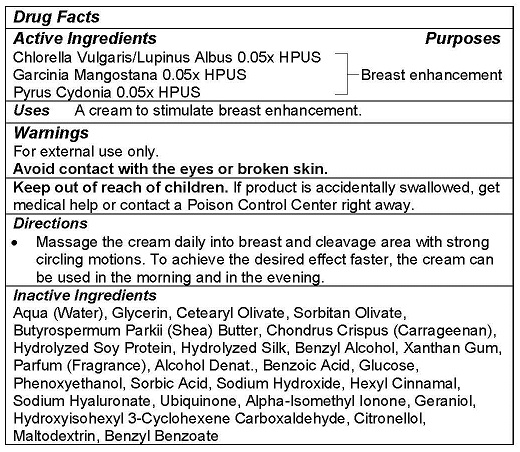 DRUG LABEL: PERFECT BUSTY BOOSTER
NDC: 71326-301 | Form: CREAM
Manufacturer: HOT PRODUCTIONS AND VERTRIEBS GMBH
Category: homeopathic | Type: HUMAN OTC DRUG LABEL
Date: 20231005

ACTIVE INGREDIENTS: CHLORELLA VULGARIS 0.05 g/100 mL; CYDONIA OBLONGA SEED 0.05 g/100 mL; GARCINIA MANGOSTANA FRUIT RIND 0.05 g/100 mL
INACTIVE INGREDIENTS: WATER; GLYCERIN; CETEARYL OLIVATE; SORBITAN OLIVATE; SHEA BUTTER; BENZYL ALCOHOL; CHONDRUS CRISPUS CARRAGEENAN; XANTHAN GUM; ALCOHOL; HYDROLYZED SOY PROTEIN (ENZYMATIC; 2000 MW); BENZOIC ACID; AMINO ACIDS, SILK; DEXTROSE, UNSPECIFIED FORM; PHENOXYETHANOL; SORBIC ACID; SODIUM HYDROXIDE; .ALPHA.-HEXYLCINNAMALDEHYDE; HYALURONATE SODIUM; UBIDECARENONE; ISOMETHYL-.ALPHA.-IONONE; GERANIOL; HYDROXYISOHEXYL 3-CYCLOHEXENE CARBOXALDEHYDE; .BETA.-CITRONELLOL, (R)-; MALTODEXTRIN; BENZYL BENZOATE

HOT PRODUCTS - Perfect Busty Booster Cream (71326-301)

ACTIVE INGREDIENTS

Chlorella Vulgaris/Lupinus Albus 0.1x HPUS

Garcinia Mangostana 0.1X HPUS

Pyrus Cydonia 0.1x HPUS

PURPOSE

Breast care.

USE

A cream to stimulate breast enhancement.

WARNINGS

For external use only.
Avoid contact with the eyes or broken skin.

Keep out of reach of children. If product is accidentally swallowed, get medical help or contact a Poison Control Center right away.

DIRECTIONS

- Massage the cream daily into breast and cleavage area with strong circling motions. To achieve the desired effect faster, the cream can be used in the morning and in the evening.

INACTIVE INGREDIENTS

Aqua (Water), Glycerin, Cetearyl Olivate, Sorbitan Olivate, Butyrospermum Parkii (Shea) Butter, Chondrus Crispus (Carrageenan), Hydrolyzed Soy Protein, Hydrolyzed Silk, Benzyl Alcohol, Xanthan Gum, Parfum (Fragrance), Alcohol Denat., Benzoic Acid, Glucose, Phenoxyethanol, Sorbic Acid, Sodium Hydroxide, Hexyl Cinnamal, Sodium Hyaluronate, Ubiquinone, Alpha-Isomethyl Ionone, Geraniol, Hydroxyisohexyl 3-Cyclohexene Carboxaldehyde, Citronellol, Maltodextrin, Benzyl Benzoate